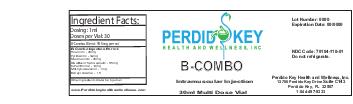 DRUG LABEL: B-Combo
NDC: 70104-110 | Form: INJECTION
Manufacturer: Perdido Key Health and Wellness Inc
Category: prescription | Type: HUMAN PRESCRIPTION DRUG LABEL
Date: 20151123

ACTIVE INGREDIENTS: METHYLCOBALAMIN 1 mg/1 mL; RIBOFLAVIN 1 mg/1 mL; NIACINAMIDE 1 mg/1 mL; DEXPANTHENOL 1 mg/1 mL; PYRIDOXINE 1 mg/1 mL; THIAMINE 1 mg/1 mL

DOSAGE FORMS AND STRENGTHS

1ml